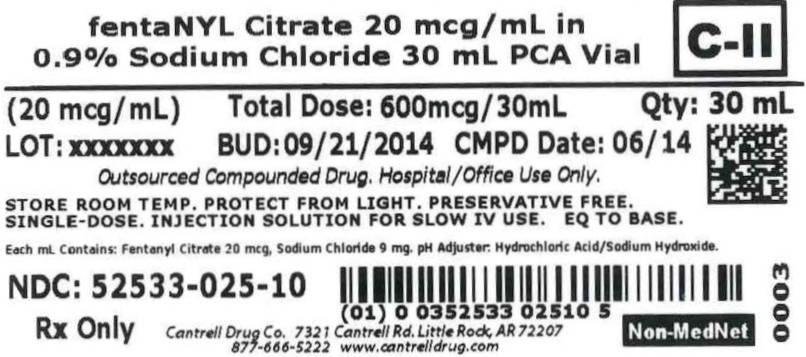 DRUG LABEL: Fentanyl Citrate
NDC: 52533-025 | Form: INJECTION, SOLUTION
Manufacturer: Cantrell Drug Company
Category: prescription | Type: HUMAN PRESCRIPTION DRUG LABEL
Date: 20140806
DEA Schedule: CII

ACTIVE INGREDIENTS: FENTANYL CITRATE 20 ug/1 mL
INACTIVE INGREDIENTS: Sodium Chloride 9 mg/1 mL; Water

Fentanyl Citrate 20 mcg/mL in 0.9% Sodium Chloride 30 mL PCA Vial, Non-MedNet